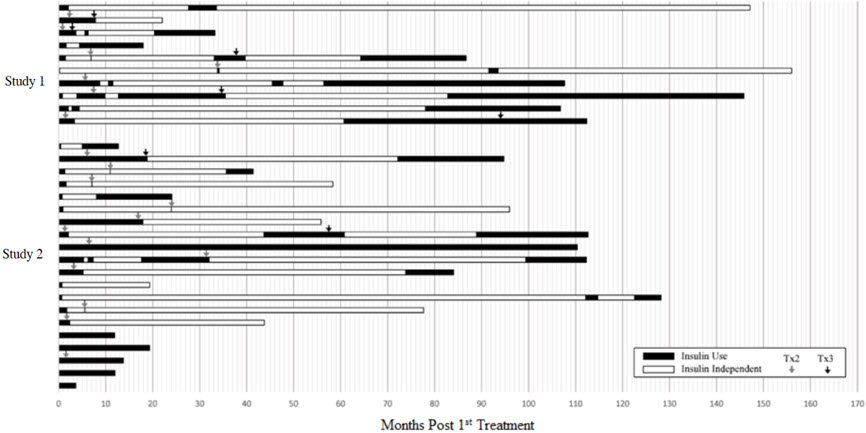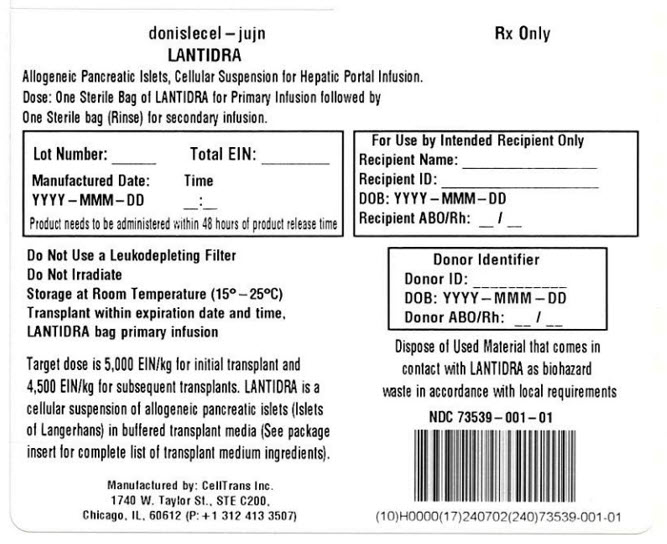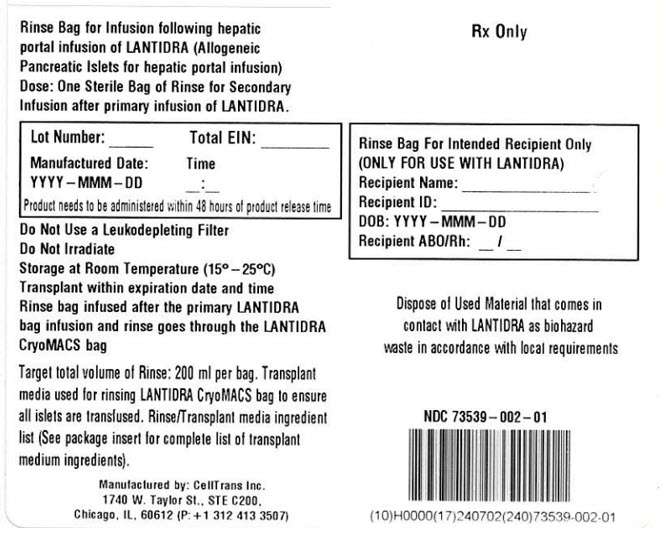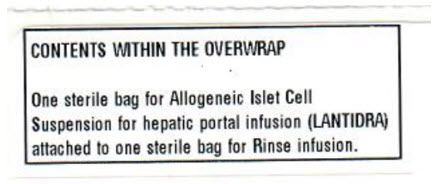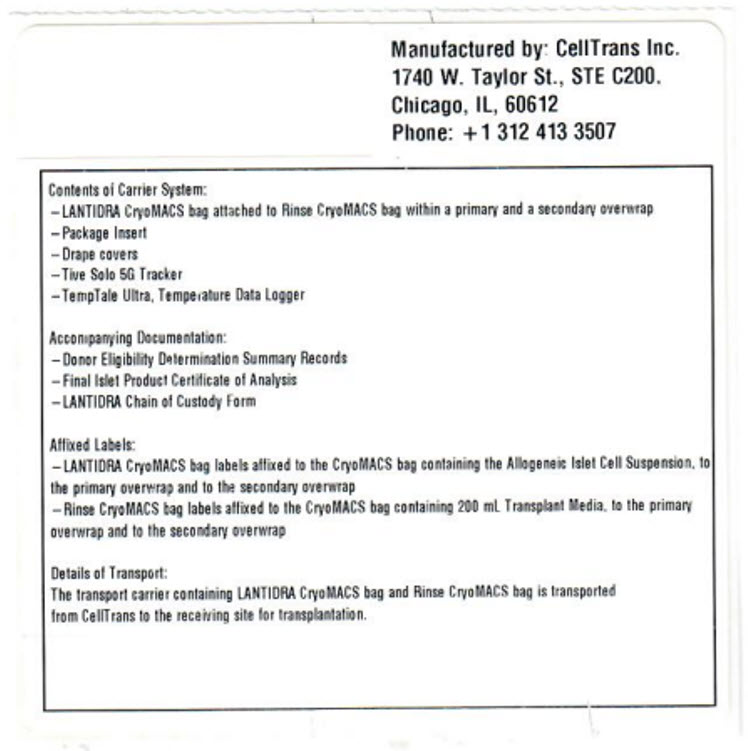 DRUG LABEL: LANTIDRA
NDC: 73539-001 | Form: SOLUTION
Manufacturer: CellTrans Inc.
Category: other | Type: CELLULAR THERAPY
Date: 20260113

ACTIVE INGREDIENTS: DONISLECEL 5000 [arb'U]/400 mL
INACTIVE INGREDIENTS: HYDROXYETHYLPIPERAZINE ETHANE SULFONIC ACID; ALBUMIN HUMAN; CALCIUM CHLORIDE ANHYDROUS; BIOTIN; MAGNESIUM SULFATE ANHYDROUS; FOLIC ACID; SODIUM ACETATE ANHYDROUS; RIBOFLAVIN; SODIUM PHOSPHATE, MONOBASIC, MONOHYDRATE; COCARBOXYLASE; ANHYDROUS DEXTROSE; COENZYME A TRILITHIUM DIHYDRATE; POTASSIUM CHLORIDE; NADIDE; SODIUM CHLORIDE; FLAVIN ADENINE DINUCLEOTIDE DISODIUM; SODIUM GLUCONATE; NADIDE PHOSPHATE MONOSODIUM; ALANINE; TRISODIUM URIDINE 5'-TRIPHOSPHATE DIHYDRATE; ARGININE HYDROCHLORIDE; ASCORBIC ACID; ASPARTIC ACID; CALCIUM PANTOTHENATE; CYSTEINE HYDROCHLORIDE; CHOLINE CHLORIDE; CYSTINE DIHYDROCHLORIDE; INOSITOL; GLUTAMIC ACID; NIACIN; GLYCINE; NIACINAMIDE; HISTIDINE MONOHYDROCHLORIDE MONOHYDRATE; AMINOBENZOIC ACID; HYDROXYPROLINE; PYRIDOXINE HYDROCHLORIDE; ISOLEUCINE; THIAMINE HYDROCHLORIDE; LEUCINE; GLUTATHIONE; LYSINE HYDROCHLORIDE; DOXRIBTIMINE; METHIONINE; 2'-DEOXYADENOSINE; PHENYLALANINE; DEOXYCYTIDINE HYDROCHLORIDE; PROLINE; 2'-DEOXYGUANOSINE; SERINE; 5-METHYLDEOXYCYTIDINE; THREONINE; CHOLESTEROL; TRYPTOPHAN; POLYSORBATE 80; VALINE; ALANYL GLUTAMINE; TYROSINE DISODIUM DIHYDRATE

HIGHLIGHTS OF PRESCRIBING INFORMATION

These highlights do not include all the information needed to use LANTIDRA safely and effectively. See full prescribing information for LANTIDRA.
LANTIDRA (donislecel-jujn) Suspension for hepatic portal vein infusion
Initial U.S. Approval: 2023

1 INDICATIONS AND USAGE

LANTIDRA is an allogeneic pancreatic islet cellular therapy indicated for the treatment of adults with Type 1 diabetes who are unable to approach target HbA1c because of current repeated episodes of severe hypoglycemia despite intensive diabetes management and education. Use in conjunction with concomitant immunosuppression. (1)

2 DOSAGE AND ADMINISTRATION

For infusion into the hepatic portal vein only.

- Do not irradiate.
- Do not use leukodepleting filters.
- Do not use if product time exceeds 48-hours post product release or if temperature is not maintained between 15 and 25° C
- To be prepared and administered only by medical professionals experienced in islet cell transplantation (2.2) (2.3)
- The recommended minimum dose is 5,000 equivalent islet number (EIN) per kg patient body weight for initial infusion (transplant) and 4,500 EIN/kg for subsequent infusions (same recipient). (2.1)
- Administer cells through the hepatic portal vein using a 5 or 6 French angiographic catheter indicated for infusion of LANTIDRA (2.3). The estimated tissue volume should not exceed 10 cc per transplant infusion. (2.1)

3 DOSAGE FORMS AND STRENGTHS

The dosage form is a cellular suspension. Dosage strength depends on the total number of islets packaged for infusion, which is reported on the container label and associated documents. (3)

4 CONTRAINDICATIONS

LANTIDRA is contraindicated in patients for whom immunosuppression is contraindicated. (4)

5 WARNINGS AND PRECAUTIONS

- Risks from Concomitant Immunosuppression: Increased risk of severe infections including opportunistic infections, malignancy, and severe anemia. Monitor closely. Administer PCP and CMV prophylaxis. (5.1)
- Procedural Complications: Liver laceration and hemorrhage have occurred. Monitor for bleeding, portal hypertension, and portal vein thrombosis during and immediately following infusion. (5.2)
- Increased Risk of Graft Rejection: Patients with a positive T- and B-cell crossmatch between recipient serum and donor lymphocytes may be at increased risk for graft rejection. (5.3)
- Transmission of Donor-Derived Infections: Monitor for signs of infection following infusion and treat accordingly. (5.4)
- Panel Reactive Antibodies (PRA): Product administration may elevate PRA and negatively impact candidacy for renal transplant. (5.5)

6 ADVERSE REACTIONS

Ninety percent (90%) of subjects had at least one serious adverse reaction. (6.1) The major causes are attributed to:

- Infusion procedure
  - liver laceration/hematoma, hemorrhage, and intra-abdominal bleeding (13%)
  - elevation of portal pressure (7%)
- Immunosuppression
  - Infection (87%)
  - Malignancy (37%)

To report SUSPECTED ADVERSE REACTIONS, contact CellTrans at 1-800-500-1617 or FDA at 1-800-FDA-1088 or www.fda.gov/medwatch.

FULL PRESCRIBING INFORMATION

1 INDICATIONS AND USAGE

LANTIDRA is an allogeneic pancreatic islet cellular therapy indicated for the treatment of adults with Type 1 diabetes who are unable to approach target HbA1c because of current repeated episodes of severe hypoglycemia despite intensive diabetes management and education. Use LANTIDRA in conjunction with concomitant immunosuppression.

Limitations of Use

When considering the risks associated with the infusion procedure and long-term immunosuppression, there is no evidence to show a benefit of administration of LANTIDRA in patients whose diabetes is well-controlled with insulin therapy or patients with hypoglycemic unawareness who are able to prevent current repeated severe hypoglycemic events (neuroglycopenia requiring active intervention from a third party) using intensive diabetes management (including insulin, devices, and education).

Repeated intraportal islet infusions are not recommended in patients who have experienced prior portal thrombosis, unless the thrombosis was limited to second- or third-order portal vein branches.

There is no evidence to support the safe and effective use of LANTIDRA in patients with liver disease, renal failure, or who have received a renal transplant.

2 DOSAGE AND ADMINISTRATION

For infusion into the hepatic portal vein only.

2.1 Recommended Dose

The recommended minimum dose is 5,000 EIN/kg for initial infusion and 4,500 EIN/kg for subsequent infusion in the same recipient. The maximum dose per infusion is dictated by the estimated tissue volume, which should not exceed 10 cc per infusion, and the total EIN present in the infusion bag (up to a maximum of 1 × 10^6 EIN per bag).

A second infusion may be performed if the patient does not achieve independence from exogenous insulin within one year of infusion or within one year after losing independence from exogenous insulin after a previous infusion. A third infusion may be performed using the same criteria as for the second infusion. There are no data regarding the effectiveness or safety for patients receiving more than three infusions.

Pre-procedural medications

Provide pre-procedural induction immunosuppression 30 – 360 minutes prior to LANTIDRA infusion. Include the following, at the discretion of the treating physician who is experienced with management of immunosuppression regimens for islet cell transplantation:

- Non-depleting monoclonal anti-interleukin-2 (anti-IL-2) receptor antibody 120 minutes prior to islet infusion
  - Note: In patients who are sensitized (hypersensitivity with a past history of anaphylactic reaction) to non-depleting monoclonal anti-interleukin-2 (anti-IL-2) receptor antibody therapies, a polyclonal, T-cell-depleting antibody should be used instead.
- Calcineurin inhibitor
- Mammalian target of rapamycin (mTOR) inhibitor
- Tumor necrosis factor (TNF) blocker.
- Periprocedural antibiotic prophylaxis is recommended.

2.2 Preparation

- Keep LANTIDRA in the insulated container at 15°C to 25°C no longer than 48 hours from time of product release (See carton label and certificate of analysis). Dispose of any product not used within 48 hours.
- Do not irradiate.
- Select and prepare units under the direction of a medical professional who is experienced in islet infusion (transplantation).
- Use LANTIDRA as supplied and without further dilution.

2.3 Administration

Failure to follow these directions may result in damage and decreased viability of the islets.

Do not administer with leukodepleting filters.

- To optimize viability, administer LANTIDRA as soon as possible after product release.
- LANTIDRA should be administered only by interventional radiologists and surgeons with experience in islet cell transplantation under aseptic conditions in an interventional radiology or operating suite.
- Perform all steps aseptically.
- Use a 5 or 6 French angiographic catheter indicated for the delivery of drugs or other therapeutic fluids for infusion of LANTIDRA.
  - Catheter length: 65 cm or less.
  - Internal diameter: 0.97mm (0.038 inches) or greater.
- Use only sheaths and introducers in combination with a catheter with the specified dimensions listed above to deliver LANTIDRA.

Pre-Infusion Patient Preparation

1. Confirm the identity of the patient for the specified unit of LANTIDRA.
2. Confirm that the patient has received appropriate premedication [See Pre-procedural medication (2.1)].
3. Confirm that appropriate medications and blood products are available to manage any potential emergencies, such as hemorrhage, portal vein thrombosis, allergic reactions, glycemic lability, bleeding, and pain.
4. Confirm that the patient is hydrated adequately prior to infusion.
5. If indicated, administer a saline/glucose infusion and administer insulin using an intravenous insulin pump during the periprocedural period.

Pre-Infusion LANTIDRA Preparation

6. Parenteral drug products should be inspected visually for particulate matter and discoloration prior to administration, whenever solution and container permit.
  a. LANTIDRA is a cellular suspension (light yellow liquid with the presence of visible cellular aggregates).
  b. The Rinse Bag contains transplant media (light yellow liquid only with no cellular aggregates present).
7. Inspect the LANTIDRA infusion bag and the Rinse Bag for leaks and breaches of container integrity.
8. Ensure the connector between the LANTIDRA infusion bag and the Rinse Bag is secure and closed.

Note: If there are any product irregularities present or if the container appears damaged or otherwise compromised, do not infuse product and immediately notify the transplant physician/team and CellTrans at 1-800-500-1617

9. Gently agitate the LANTIDRA infusion bag to ensure that the islets are suspended and to prevent clumping. Do not shake the bag, as this may damage the islets. Repeat gentle agitation periodically throughout the infusion process.
10. Remove the first drape bag and transfer the product to an infusion operator to remove the second drape bag.
11. Ensure that the intravenous tubing is closed, then connect the LANTIDRA infusion bag, fill the drip chamber, and open the roller clamp to fill the tubing and remove air.

LANTIDRA Infusion Procedure

12. Insert the catheter into the portal vein.
13. Once the catheter placement in the portal vein is confirmed, connect the intravenous tubing from the LANTIDRA infusion bag to the catheter using a Luer lock connector.
14. Infuse all infusion bags by gravity flow over approximately 30 minutes at rates ≤ 25 mL/kg/h.
15. Flush the infusion lines periodically to clear them.
16. Do not administer LANTIDRA (islet cell product and rinse bag) through intravenous lines that contain any other medications or infusates other than physiological saline.
17. Reduce infusion rate if the fluid load is not tolerated.
18. Discontinue the infusion in the event of an allergic reaction or if the patient develops a moderate to severe infusion reaction.
19. Once the islet infusion is complete, open the roller clamp on the Rinse Bag tubing to allow refilling and rinsing of the LANTIDRA infusion bag. Gently agitate the LANTIDRA infusion bag with small amounts of rinse solution to ensure that all cells have been administered. Repeat until the Rinse Bag is empty.
20. Withdraw the catheter tip from the main portal vein into the liver parenchyma until it lies within a few centimeters (cm) of the liver capsule. Before withdrawing the catheter completely, manage hemostasis in the catheter track using standard practices to reduce the risk of bleeding.

Monitoring during LANTIDRA Infusion

- Measure portal pressure during the infusion.
  - Pause infusion if portal pressure rises above 22 mmHg and do not resume until it falls below 18 mmHg.
  - Terminate infusion if portal pressure remains above 22 mmHg for longer than 10 minutes.
- Monitor blood glucose levels every 15 minutes during the infusion and then every 30 minutes for the first 4 to 8 hours after infusion. Provide appropriate treatment if blood glucose levels fall below 70 mg/dL. Monitor blood glucose levels as needed once blood glucose levels have stabilized. After the acute period (first 4 to 8 hours following infusion), continue to monitor blood glucose (laboratory, capillary blood glucose, or continuous glucose monitor). Only use blood glucose meters and continuous glucose monitoring systems labelled for use in the hospital.
- Monitor the patient for portal vein branch thrombosis. Early diagnosis and prompt management with systemic heparinization may prevent clot propagation. However, anticoagulation therapy may lead to intra-abdominal hemorrhage requiring blood transfusion and surgical intervention.

Post-Infusion

- Monitor the patient in hospital for a minimum of 24 hours.
- Perform an abdominal ultrasound and Doppler examination of the liver after catheter removal to detect portal vein thrombosis and intra-abdominal bleeding. Repeat these examinations at least on days 1 and 7 post infusion procedure.
- Continue to monitor the patient for adverse reactions.
- Continue to monitor blood glucose levels following infusion and manage according to inpatient standard of care.

Post-Infusion Medications

- Anti-infective medications: Administer Pneumocystis jirovecii pneumonia (PCP) and cytomegalovirus (CMV) prophylaxis immediately following infusion of LANTIDRA and continue treatment as described in the prescribing information for the specific anti-infective medications.
- A non-depleting monoclonal anti-IL-2 receptor antibody: Administer at Week 2 after infusion for a total of two (2) doses, except in sensitized patients, who should instead be administered a polyclonal, T-cell-depleting antibody.
- Tumor necrosis factor (TNF) blocker: Administer on post-infusion Days 3, 7, and 10.

Long-term Medications

Immunosuppression: Continue immunosuppression permanently to prevent islet graft rejection. [See Warnings and Precautions (5.1)]. (See Section 5.1 for reasons to discontinue immunosuppression.)

Avoid systemic steroids. Use a combination of a calcineurin inhibitor and an mTOR inhibitor or appropriate alternatives, at the discretion of the physician. Monitor trough levels of maintenance immunosuppressant drugs, and adjust the dose to maintain appropriate blood levels.

3 DOSAGE FORMS AND STRENGTHS

LANTIDRA is a cellular suspension of allogeneic pancreatic islets (islets of Langerhans) in buffered transplant media containing sodium chloride, dextrose, minerals, amino acids, vitamins, and other compounds supplemented with HEPES (2-[4-(2-hydroxyethyl)piperazin-1-yl] ethanesulfonic acid; 10 mM final concentration) and human serum albumin (0.5% final concentration).

Each infusion uses one lot of LANTIDRA which consists of islets manufactured from the pancreas of a single deceased donor. Each dose of LANTIDRA is provided as two (2) infusion bags connected to each other via sterile connector. One bag contains LANTIDRA up to a maximum of 1 × 10^6 EIN in 400 ml of transplant media and the second bag (Rinse Bag) contains transplant media used to rinse the LANTIDRA bag and the infusion line.

The dosage strength is represented by the total EIN in a single preparation and varies between product batches. Dosage strength information for an individual batch is provided on the container label and in accompanying documentation (Final Islet Product Certificate of Analysis).

4 CONTRAINDICATIONS

Do not administer LANTIDRA to patients who have concomitant diseases or conditions, including pregnancy, that contraindicate the procedure for LANTIDRA infusion or immunosuppression.

5 WARNINGS AND PRECAUTIONS

5.1 Risks from Concomitant Immunosuppression

Concomitant use of immunosuppression is required to maintain islet cell viability. The use of immunosuppression in patients receiving LANTIDRA increases the risk of serious and potentially fatal adverse reactions. [Adverse Reactions (6.1)]

Patients receiving immunosuppressants are at increased risk of:

- Bacterial, viral, fungal, and parasitic infections, including opportunistic infections.
- Lymphomas and other malignancies, particularly of the skin.
- Severe anemia, sometimes requiring transfusion.

Before Treatment

- Vaccination: To mitigate the risk of infection, patients should receive recommended immunizations prior to treatment.

After Treatment

- Administer PCP and CMV prophylaxis following administration of LANTIDRA.
- Avoid live vaccination while receiving immunosuppression.
- Monitor for fever and other signs of infection; initiate appropriate treatment early.
- Clinically monitor for malignancy, including skin cancer.
- Monitor hemoglobin/hematocrit and give blood products as indicated.

Considerations for discontinuation of immunosuppression

- If a patient develops a life-threatening infection or cancer and treatment requires discontinuation of immunosuppression.
- If a patient has been dependent on exogenous insulin for two years after their last infusion, then immunosuppression should be discontinued. However, the treatment team may consider continuation of immunosuppression if they determine that the patient has achieved target HbA1c without recurrent severe hypoglycemia in the presence of clinically relevant C-peptide, that provides a potential ongoing benefit that outweighs the risks of severe and potentially life-threatening effects of immunosuppression.
- If a patient becomes pregnant.

5.2 Procedural Complications

Liver laceration, hemorrhage and intra-abdominal bleeding have occurred with portal administration of LANTIDRA. Manage hemostasis in the catheter track using standard practices following infusion of LANTIDRA to reduce the risk of bleeding. Monitor for bleeding clinically and with laboratory assessments. Blood transfusions have been required.

Elevation in portal blood pressure has occurred during and following intraportal islet infusion [Adverse Reactions (6.1)]. Monitor portal pressure; pause infusion if portal pressure rises above 22 mmHg and do not resume until it falls below 18 mmHg. Terminate infusion if portal pressure remains above 22 mmHg for longer than 10 minutes. [Dosage and Administration (2.3)]

Portal vein branch thrombosis may occur following infusion of LANTIDRA. Repeated intraportal islet infusions are not recommended in patients who have experienced prior portal thrombosis unless the thrombosis was limited to second- or third-order portal vein branches. [Limitations of Use (2.1)]

5.3 Increased Risk of Islet Graft Rejection

Patients with a positive T- and B-cell crossmatch between recipient serum and donor lymphocytes may immediately reject the islet cells. The T- and B-cell crossmatch assay is binary. T- and B-cell both need to be negative.

5.4 Transmission of Donor-Derived Infections

There is a risk of communicable disease transmission from donor to recipient that exists for LANTIDRA. Monitor patients for signs of active infection following LANTIDRA infusion and treat appropriately if infection is suspected.

5.5 Panel Reactive Antibodies (PRA)

Product administration may elevate PRA and negatively impact candidacy for renal transplant. Consider benefit-risk of administering LANTIDRA to a patient who may require a renal transplant in the future.

6 ADVERSE REACTIONS

Ninety percent (90%) of subjects had at least one serious adverse reaction. The major causes were attributed to:

- Infusion procedure
  - liver laceration/hematoma, hemorrhage, and intra-abdominal bleeding (13%)
  - elevation of portal pressure (7%)
- Immunosuppression
  - Infection (87%)
  - Malignancy (37%)

6.1 Clinical Trials Experience

Because clinical trials are conducted under widely varying conditions, adverse reaction rates observed in the clinical trials of a drug cannot be directly compared to rates in the clinical trials of another drug and may not reflect the rates observed in practice.

The safety of LANTIDRA in subjects with type 1 diabetes and hypoglycemic unawareness was demonstrated in two clinical trials (Study 1, Study 2) involving a total of 30 subjects who received between one and three doses of LANTIDRA. Duration between first and second transplant was one month to 2.8 years and between second and third dose from 3 months to 7.8 years (See Figure 1). Because of the variable duration of follow-up, number of infusions, and interval between infusions, adverse reactions were reported for the total duration for which each subject was followed. [Clinical Studies (14)] Subjects were followed for 0.3 to 14.5 years (mean 3 ± 3.7 years) after the first infusion.

Serious reactions were reported in 27 (90%) of subjects. There were two (7%) deaths; one death from multi-organ failure with sepsis (1.6 years after the first infusion), and one from progressive confusion, global atrophy and micro-ischemic disease (9.7 years after the first infusion). Both subjects were using immunosuppression at the time of the event. Additionally, 8 (27%) subjects experienced at least one life-threatening adverse reaction and 26 (87%) subjects experienced at least one severe reaction before their last follow-up.

Immunosuppression-Related Adverse Reactions

Risks of common community-acquired infections and opportunistic infections increases with immunosuppression. In total, 211 infections were reported for 26 subjects; one was life-threatening, 22 reactions severe, and 115 events moderate in severity. Additionally, one subject died of multi-organ failure from sepsis in the second year after infusion.

Discontinuation of immunosuppression resulted in loss of islet cell function and if achieved insulin independence. This was described for 8 (27%) subjects.

Malignancy risk is known to increase with immunosuppression. In total, 16 adverse reactions of malignancy were reported in 11 subjects; three malignancies were life-threatening. The malignancies included 12 skin cancers, and one post-transplant lymphoproliferative disease, one breast cancer, and one thyroid cancer. Anemia was reported in 24 (80%) of subjects. Of the 90 adverse reactions reported, one reaction was life-threatening (Hgb <6.5gm/dL), 9 reactions were severe (<8-6.5 gm/dL), and 27 reactions were moderate in severity (<10-8 gm/dL).

Anemia was attributed to bleeding because of procedural complications as well as immunosuppression. Transfusion was required for severe and life-threatening reactions. Overall, five transfusions were administered to five subjects. Three transfusions were for procedural related complications and two were non-procedure related. Alterations in red blood cell turnover and transfusion can alter the accuracy of HbA1c measurements. Therefore, in addition to monitoring for the development of anemia as a result of immunosuppression or a result of a procedural complications, healthcare providers should consider the occurrence of anemia in the interpretation and use of HbA1c in the management of patients with type 1 diabetes who have received LANTIDRA.

Procedural Complications

Serious reactions related to the 56 infusion procedures included one life-threatening liver laceration, one intraabdominal hemorrhage, and two perihepatic hematomata resulting in prolonged hospitalization. Manage hemostasis in the catheter track using standard practices following infusion of LANTIDRA to reduce the risk of bleeding.

Elevation in portal blood pressure may occur following intraportal islet infusion but is usually temporary. During clinical trials with LANTIDRA, the median peak portal blood pressure increase from baseline was 3 mmHg (range -3 to 18 mmHg). Elevated portal pressures ≥ 22 mmHg were reported during procedures for two subjects requiring cessation of the procedure, and incomplete delivery of LANTIDRA for one subject. Monitor portal pressure and halt islet infusion if portal pressure rises above 22 mmHg.

Panel Reactive Antibodies

Of the 30 subjects who received LANTIDRA, 28 subjects had panel reactive antibody (PRA) data. Overall, 6 of 28 (21%) had a transition from baseline Class I PRA < 20% to ≥ 20% after infusion. These included 1 of 9 (11%) who received one infusion, 3 of 12 (25%) who received two infusions, and 2 of 7 (29%) who received three infusions.

Table 1: Adverse Reactions Occurring in ≥20% of Subjects, with some Subjects Experiencing Grade 3 Adverse Events (reactions) from Initial Infusion (Transplant) through 1 Year After Final Infusion (Transplant) (Study 1 and Study 2; 30 Subjects)
Adverse Reaction | % Subjects Any Severity | % Treated Subjects Severity ≥ Grade 3*
Nausea | 83 | 7
Fatigue | 83 | 3
Anemia | 80 | 27
Diarrhea | 80 | 13
Abdominal pain | 67 | 7
Asthenia (loss of overall energy) | 67 | 7
Headache | 67 | 3
Hyponatremia (low levels of sodium) | 63 | 13
Transaminases increased | 63 | 7
Upper respiratory tract infection | 63 | 3
Vomiting | 60 | 7
Urinary tract infection | 53 | 10
Hypoalbuminemia (low levels of albumin) | 47 | 3
Low density lipoprotein increased | 43 | 37
Myalgia (muscle pain) | 43 | 3
Sinusitis | 40 | 7
Chills | 40 | 3
Hemoglobin decreased | 37 | 3
Tinnitus | 30 | 3
Decreased appetite | 27 | 3
Hypertension | 23 | 7
Pneumonia | 20 | 17
Hypercholesterolemia (increased cholesterol) | 20 | 3
Depression | 20 | 3
Menstruation irregular | 20 | 3
Common Terminology Criteria for Adverse Events (CTCAE) Version 5
Grade 3: (Severe) Severe or medically significant but not immediately life-threatening; hospitalization or prolongation of hospitalization indicated; disabling; limiting self-care activities of daily living.
Grade 4: (Life-threatening) consequences; urgent intervention indicated.
Grade 5: Death related to the adverse event.

Common adverse reactions (occurring in ≥20% but ≤ 90% of subjects) independent of severity observed between initial infusion and 1 year following final infusion include:

Blood and lymphatic system disorders: anemia, leukopenia

Cardiac disorders: palpitations

Ear and labyrinth disorders: ear pain, tinnitus

Eye disorders: eye pain, vision blurred

Gastrointestinal disorders: abdominal pain, diarrhea, dry mouth, mouth ulceration, nausea, stomatitis, vomiting

General disorders and administration site conditions: asthenia, chills, edema peripheral, fatigue, feeling cold, thirst

Hepatobiliary disorders: hepatic steatosis, hyperbilirubinemia

Infections and infestations: herpes zoster, pneumonia, sinusitis, upper respiratory tract infection, urinary tract infection

Injury, poisoning and procedural complications: contusion

Investigations: aspartate aminotransferase increased, blood bicarbonate decreased, blood cholesterol increased, hemoglobin decreased, low density lipoprotein increased, transaminases increased

Metabolism and nutrition disorders: abnormal loss of weight, anorexia and bulimia syndrome, appetite disorder, decreased appetite, hypercholesterolemia, hyperkalemia, hypoalbuminemia, hypocalcemia, hypomagnesemia, hyponatremia

Musculoskeletal and connective tissue disorders: arthralgia, muscle spasms, musculoskeletal stiffness, myalgia, pain in extremity

Neoplasms benign, malignant and unspecified (including cysts and polyps): thyroid neoplasm

Nervous system disorders: disturbance in attention, dizziness, headache, hypoesthesia, tremor

Psychiatric disorders: anhedonia, anxiety, depressed mood, depression, insomnia, nervousness

Renal and urinary disorders: hematuria, hypertonic bladder, nocturia, pollakiuria, urinary incontinence

Reproductive system and breast disorders: menstruation irregular

Respiratory, thoracic and mediastinal disorders: cough, dysphonia, dyspnea, nasal congestion, oropharyngeal pain, sinus disorder

Skin and subcutaneous tissue disorders: acne, dry skin, onychoclasis, pruritus, rash

Vascular disorders: hypertension

Less common adverse reactions (occurring in ≥5% but <20% of subjects) observed between initial infusion and 1 year following final infusion include:

Blood and lymphatic system disorders: increased tendency to bruise, lymphadenopathy, neutropenia, thrombocytopenia

Cardiac disorders: myocardial ischemia

Ear and labyrinth disorders: deafness, vertigo

Endocrine disorders: hypoglycemia, thyroid cyst

Eye disorders: cataract, conjunctival hemorrhage, eye edema, eye pruritus

Gastrointestinal disorders: Barrett's esophagus, bowel movement irregularity, colitis, constipation, dyspepsia, gastroesophageal reflux disease, oral pain, toothache

General disorders and administration site conditions: catheter site pain, chest pain, feeling of body temperature change, gait disturbance, influenza like illness, injection site extravasation, mucosal inflammation, pain, pyrexia

Hepatobiliary disorders: cholelithiasis

Immune system disorders: sensitization

Infections and infestations: bacterial vaginosis, cellulitis, cytomegalovirus infection, ear infection, Epstein-Barr infection, eye infection, fungal infection, gastroenteritis, gastroenteritis viral, localized infection, nail infection, nasopharyngitis, onychomycosis, oral candidiasis, oral herpes, osteomyelitis, rhinitis, tooth infection, vaginal infection, viral upper respiratory tract infection, vulvovaginal mycotic infection

Injury, poisoning and procedural complications: hepatic hematoma, limb injury, meniscus injury

Investigations: alanine aminotransferase increased, blood alkaline phosphatase increased, blood creatinine increased, glomerular filtration rate decreased, neutrophil count decreased, urine albumin/creatinine ratio, urine protein/creatinine ratio increased, weight decreased, weight increased

Metabolism and nutrition disorders: dehydration, hyperchloremia, hyperlipidemia, hypertriglyceridemia, hypokalemia, hypophosphatemia

Musculoskeletal and connective tissue disorders: arthritis, back pain, intervertebral disc protrusion, joint stiffness, joint swelling, muscular weakness, musculoskeletal pain, neck pain, osteoarthritis, osteopenia, osteoporosis

Neoplasms benign, malignant and unspecified (including cysts and polyps): basal cell carcinoma, squamous cell carcinoma

Nervous system disorders: carpal tunnel syndrome, cognitive disorder, dysgeusia, dyskinesia, head titubation, migraine, neuropathy peripheral, paresthesia, poor quality sleep, sinus headache, syncope

Psychiatric disorders: agitation, decreased interest, libido decreased

Renal and urinary disorders: hemoglobinuria, hydronephrosis, proteinuria, urine flow decreased

Reproductive system and breast disorders: erectile dysfunction, menorrhagia, vaginal hemorrhage

Respiratory, thoracic and mediastinal disorders: dyspnea exertional, epistaxis, pleural effusion, rhinorrhea, wheezing

Skin and subcutaneous tissue disorders: alopecia, dermatitis, erythema, hidradenitis, nail disorder, night sweats, rash pruritic, rosacea, skin exfoliation, skin lesion

Vascular disorders: peripheral artery stenosis

8 USE IN SPECIFIC POPULATIONS

8.1 Pregnancy

Risk Summary

Pregnancy risk has not been assessed for LANTIDRA. No animal reproductive and development toxicity studies have been conducted with LANTIDRA. However, there is a risk of fetal malformations associated with certain immunosuppression medications that may be used following LANTIDRA administration. Additionally, the risks to the patient and fetus from the procedure for LANTIDRA infusion in pregnant women has not been assessed.

In the U.S. general population, the estimated background risk of major birth defects and miscarriage in clinically recognized pregnancies is 2-4% and 15-20%, respectively.

8.2 Lactation

Risk Summary

The risk of exposing a child to LANTIDRA components during breastfeeding has not been assessed. However, some required concomitant medications, including immunosuppressants, may be excreted in milk at least in trace amounts. Because of this, a decision should be made about whether to discontinue breastfeeding in patients who will receive a LANTIDRA infusion.

8.3 Females and Males of Reproductive Potential

Pregnancy Testing

Due to the risk of fetal malformations associated with required concomitant medications, including immunosuppressants, females of reproductive potential should have a confirmed negative pregnancy test prior to LANTIDRA infusion.

Female patients of reproductive potential should be counselled to contact their transplant team immediately if they become pregnant.

Contraception

Because long-term immunosuppression is required following LANTIDRA administration, women of childbearing potential should be informed of the potential risks that these medications pose during pregnancy and should be told to use effective contraception prior to initiation of immunosuppression and thereafter for as long as they retain reproductive potential.

Infertility

Male and female fertility may be compromised by certain medications used for maintenance immunosuppression following LANTIDRA administration.

For male patients, review the concomitant medications and determine if there is a potential for production of abnormal sperm.

8.4 Pediatric Use

The safety and effectiveness of LANTIDRA have not been established in pediatric patients with type 1 diabetes.

8.5 Geriatric Use

The safety and effectiveness of LANTIDRA have not been established in geriatric patients with type 1 diabetes and hypoglycemic unawareness. Clinical studies of LANTIDRA did not include sufficient numbers of patients aged 65 and over to determine whether they respond differently than younger patients.

11 DESCRIPTION

LANTIDRA consists of a suspension of allogeneic pancreatic islets in buffered transplant medium containing sodium chloride, dextrose, minerals, amino acids, vitamins, and other compounds supplemented with HEPES (2-[4-(2-hydroxyethyl)piperazin-1-yl] ethanesulfonic acid; 10 mM final concentration) and human serum albumin (0.5% final concentration).

The active ingredient in LANTIDRA is allogeneic islets of Langerhans derived from a donor pancreas. Islets contain several types of endocrine (hormone-secreting) cells, including β-, α-, pancreatic peptide- (PP-), δ-, and ε-cells.

Each single-donor islet batch consists of two infusion bags connected to each other via a sterile connector. One LANTIDRA bag containing up to a maximum of 1 × 10^6 EIN in 400 ml of transplant media, and the second Rinse Bag containing 200 ml transplant media used to rinse the LANTIDRA bag and the infusion line.

Ingredients present in transplant media are:

CaC12, anhydrous, biotin, MgSO4, anhydrous, folic acid, Na acetate, anhydrous, riboflavin, NaH2PO4H2O, cocarboxylase, dextrose, Li3 coenzyme A 2 H2O, KCl, cozymase, NaCl, Na2 flavin adenine dinucleotide, Na gluconate H2O, Na triphosphopyridine nucleotide, L-alanine, Na3 uridine 5'-triphosphoric acid H2O, L-arginine HCl, ascorbic acid, L-aspartic acid, D-Ca-pantothenate, L-cysteine HCl H2O, choline chloride, L-cystine 2 HCl, i-inositol, L-glutamic acid, nicotinic acid, glycine, nicotinamide, L-histidine HCl H2O, para-aminobenzoic acid, hydroxy-L-proline, pyridoxine HCl, L-isoleucine, thiamine HCl, L-leucine, glutathione (reduced), L-lysine HCl, thymidine, L-methionine, 2D-adenosine, L-phenylalanine, 2D-cytidine HCl, L-proline, 2D-guanosine, L-serine, 5-methyl-2'- deoxycytidine, L-threonine, cholesterol, L-tryptophan, Tween 80, L-valine, L-alanyl-L-glutamine, L-tyrosine 2 Na 2 H2O

12 CLINICAL PHARMACOLOGY

12.1 Mechanism of Action

Pancreatic islets regulate blood glucose levels through secretion of multiple hormones in response to increases and decreases in blood glucose. Endocrine cells within pancreatic islets release insulin, glucagon, somatostatin, pancreatic peptide, and ghrelin. Insulin stimulates glucose uptake by peripheral tissues; glucagon mobilizes glucose from the liver into circulation; somatostatin inhibits both α- and β-cell secretions; pancreatic peptide inhibits pancreatic exocrine secretion; and ghrelin inhibits insulin secretion. The primary mechanism of action of LANTIDRA is believed to be secretion of insulin by infused (transplanted) β- cells.

12.2 Pharmacodynamics

The pharmacodynamic effects of LANTIDRA are a result of hormones, especially insulin, that are secreted by the infused (transplanted) islets in response to fluctuations in blood glucose levels.

Basal and stimulated blood glucose were determined at baseline and at 1 year following a subject's last transplant during Study 1 and Study 2 using a mixed meal tolerance test (MMTT). Combined results from these studies are summarized in Table 2. [Clinical Studies (14)]

The pharmacodynamic profile of the allogeneic islet cells is most clearly demonstrated in subjects who are free from the requirement of exogenous insulin.

TABLE 2: Effect of donislecel on Levels of Blood Glucose (mg/dl) at Baseline and 1 Year After Final Infusion (Study 1 and Study 2) for Subjects Insulin-Independent at the time of Mixed Meal Tolerance Test (MMT).
Subjects Insulin Independent at time of 1-year MMT | N | Mean (mg/dl) | Std Dev (mg/dl) | Min (mg/dl) | Max (mg/dl)
Baseline Glucose Basal | 19 | 178 | 76 | 78 | 348
Baseline Glucose 90-min | 19 | 357 | 91 | 122 | 559
1-year Glucose Basal | 19 | 106 | 17 | 81 | 144
1-year Glucose 90-min | 19 | 142 | 40 | 65 | 202

14 CLINICAL STUDIES

The effectiveness of LANTIDRA in subjects with type 1 diabetes and hypoglycemic unawareness was demonstrated in 2 clinical trials (Study 1, Study 2) involving a combined 30 subjects, all of whom received at least one islet infusion and a maximum of 3 infusions. Both trials were prospective, open-label, single-arm studies.

Subject demographics: median age 46.5 (range: 21 – 67) years, 80% female, 100% white, 97% non-Hispanic.

Subjects received a median islet number of 399,178 EIN (range 253,924 EIN to 858,856 EIN) per infusion. Subjects received a median islet dose of 6,570 EIN/kg (range 4,186 EIN/kg to 13,633 EIN/kg) per infusion. Thirty subjects participated in the combined Study 1 and Study 2, with 11 subjects receiving one infusion, 12 subjects receiving two infusions, and 7 subjects receiving three infusions. Of the 19 subjects who received a second infusion, 6 were insulin-independent at the time of their second infusion. Of the 11 subjects who did not receive a second infusion, 4 were insulin-independent, 3 did not have a donor, and 4 were intolerant to immunosuppression or withdrew from the study within 6 months. All 7 subjects who received a third infusion were insulin-dependent. One subject was not able to get a third infusion because of infection. No subject was unable to receive a third infusion because of lack of a donor or intolerance to immunosuppression.

Concomitant study medications were provided as described in Table 3:

Table 3: Summary of Administered Concomitant Study Medications
Medication | Study 1 (N=10) | Study 2 (N=20)
Anakinra; n (%) | 1 (10%) | 0 (0%)
Daclizumab; n (%) | 10 (100%) | 5 (24%)
Basiliximab; n (%) | 5 (10%) | 19 (95%)
Mycophenolate mofetil; n (%) | 6 (60%) | 5 (24%)
Etanercept; n (%) | 6 (60%) | 20 (100%)
Everolimus; n (%) | 1 (10%) | 2 (10%)
Sirolimus; n (%) | 10 (100%) | 20 (100%)
Tacrolimus; n (%) | 10 (100%) | 20 (100%)
Cyclosporine; n (%) | 1 (10%) | 3 (15%)
Anti-thymocyte immunoglobulin; n (%) | 1 (10%) | 4 (20%)

A glucagon-like peptide-1 (GLP-1) agonist (e.g., exenatide 5 mcg subcutaneously within 60 minutes before infusion), was administered and was supposed to be continued (5 mcg BID), for up to 6 months after transplant. Exenatide was not given to the first 4 subjects in Study 1, and 11 of the remaining 26 subjects used exenatide less than the per protocol 6-months post-transplant because of adverse reactions. Because of the variability of exenatide use in the clinical studies, there are insufficient data to support exenatide use in patients receiving LANTIDRA.

Insulin independence, defined as not requiring exogenous insulin to achieve adequate glycemic control, was also determined. Results are summarized in Table 4.

Table 4: Achievement and Maintenance of Glycemic Control following LANTIDRA Infusion (Studies Study 1 and Study 2)
Total Duration Insulin Independent (years) | N | Mean | Std Dev | Min | Max
Study 1 | 10 | 5.1 | 4.2 | 0.2 | 12.8
Study 2 | 20 | 3.2 | 3.1 | 0 | 9.9

Five subjects had no days of insulin independence. For the 25 subjects who achieved insulin independence, 4 subjects (13.3%) were insulin independent for less than one year, 12 subjects (36.7%) for 1 to 5 years, and 9 subjects (33.3%) for greater than 5 years. Figure 1 shows the entire experience of the individual subjects.

Figure 1: Periods of Insulin Use and Insulin Independence following Initial Infusion, by Patient (Pooled Population)

This figure shows the total duration of follow-up for each subject. The period of insulin dependence (use) is denoted in black and the period of insulin independence in white. Time zero (0) is the time of the first infusion. The arrows denote the time of second and third infusions.

16 HOW SUPPLIED/STORAGE AND HANDLING

LANTIDRA (NDC 73539-001-01) is supplied as purified allogeneic islets of Langerhans suspended in buffered transplant medium containing sodium chloride, dextrose, minerals, amino acids, vitamins, and other compounds supplemented with HEPES (2-[4-(2-hydroxyethyl)piperazin-1-yl] ethanesulfonic acid; 10 mM final concentration) and human serum albumin (0.5% final concentration)). [Description (11)].

LANTIDRA is contained in one 1000 mL infusion bag filled with a supplied volume of 400 mL, containing not more than 10 cc of estimated packed islet tissue and not more than 1 × 10^6 EIN. The 1000 mL infusion bag is aseptically connected to a smaller 750 mL Rinse Bag (NDC 73539-002-01) containing 200 mL of supplied volume of transplant media for use in rinsing the 1000 mL bag containing LANTIDRA and infusion line following infusion to assure complete transfer of islets to the patient. Additional product information, including islet number, is included on the Final Islet Product Certificate of Analysis and the container label.

STORAGE AND HANDLING

- Store in the insulated container at 15°C to 25°C for up to 48 hours from time of product release.
- Dispose used bags and infusion lines as biohazard material.

17 PATIENT COUNSELING INFORMATION

Advise the patient to read the FDA-approved patient labeling (Patient Information).

Prior to prescribing LANTIDRA discuss the following:

Procedural risks

- Portal vein delivery
  - liver laceration and hematoma with severe, potentially life-threatening bleeding, which may require prolonged hospitalization and blood transfusions
  - liver injury from portal vein thrombosis and possible portal hypertension
- Acute infusion reaction
  - symptoms may include fever, chills, fatigue, breathing problems, dizziness, nausea, vomiting, headache, or muscle aches
  - a minimum 24-hour stay in the hospital after the procedure will be required for monitoring

Immunosuppression requirements and risks

- Treatment with immunosuppression
  - Is required long-term
  - If stopped would lead to loss of islet cell function and insulin production
  - Can interfere with response to immunizations and that they should avoid live vaccines
- Increased risk of infection
  - Infections can be severe and life-threatening
  - Infections may require withdraw of immunosuppression
- Development of lymphoma and other malignancies
  - Skin malignancies are most common
  - Lymphoma and some malignancies may require discontinuation of immunosuppression
- Can interfere with usual response to immunizations
  - Patients should receive all appropriate immunizations prior to treatment.

Requirements for ongoing diabetes management and risks

- Not all patients who receive LANTIDRA are able to achieve independence from exogenous insulin (stop insulin injections).
- Not all patients who achieve independence from exogenous insulin can maintain this independence.
- Continued blood glucose monitoring is required after the procedure. Advise patient to follow all instructions regarding glucose monitoring from their endocrinologist and transplant physician.
  - Failure to perform continued monitoring can increase the risk of hypoglycemia and hyperglycemia.
- Continued insulin treatment is required after the procedure. Advise patient to follow all instructions regarding insulin dosing from their endocrinologist and transplant physician.
  - Failure to continue or restart insulin when required puts patients at risk for severe and potentially life-threatening hyperglycemia, including diabetic ketoacidosis (DKA).
  - Patients should seek emergency medical care for severe hypoglycemic episodes and DKA.

Considerations for pregnancy, lactation, and infertility

Pregnancy

- Inform female patients who are of childbearing potential that immunosuppressive drugs required to maintain islet cell survival can cause serious harm, including malformations in the fetus.
  - Advise female patients that if they are able to become pregnant, then they should use effective birth control.
  - Advise female patients to notify their endocrinologist and transplant physician if they become pregnant.
- Inform male patients receiving LANTIDRA who have female partners who are able to become pregnant that they should use effective birth control before and during treatment.
  - If applicable, advise male patients whose partner becomes pregnant, to inform her that she should seek medical advice from her healthcare provider.

Lactation

If the immunosuppressive drugs have the potential to affect the ability of the patient to breast feed, inform the patient that breast feeding would be discontinued prior to starting the pre-procedural medications needed for administration of LANTIDRA.

Fertility

Inform patients that treatment with immunosuppression drugs may impair fertility and the ability to achieve pregnancy in the future.

Considerations for future transplants

Inform patients that administration of LANTIDRA has been associated with the development of panel reactive antibodies (PRA). PRA can adversely affect the ability to achieve a donor match for those patients who require kidney transplant.

After infusion of LANTIDRA, discuss the following:

In preparation for discharge after the procedure and at appropriate follow up appointments, repeat the information for immunosuppression, diabetes management, reproductive considerations (pregnancy, lactation, and fertility).

Manufactured by:
CellTrans Inc.
2201 W. Campbell Park Drive
Chicago, IL 60612
24-Hour Contact Phone Number: 800-500-1617

© CellTrans

Patient Information

LANTIDRA (donislecel-jujn)
Allogeneic Pancreatic Islet Cellular Suspension for Hepatic Portal Vein Infusion

Read this patient information before you start treatment with LANTIDRA. There may be new information.

This information does not take the place of talking with your healthcare provider about your medical condition, your treatment options or the potential benefits and risks of treatment with LANTIDRA.

What is the most important information I should know about LANTIDRA?

LANTIDRA is only for adult patients with Type 1 diabetes who have repeated episodes of severe low blood glucose, those that they need help from someone to treat, and cannot get their HbA1c at the goal set by their endocrinologist and diabetes team, despite intensive diabetes management and education.

LANTIDRA is a cell therapy that is infused (transplanted) into your liver. Talk to your transplant doctor or endocrinologist about your risks from the infusion procedure and the long-term immune suppression medicine that you will need to use after you get the infusion.

Risks from the infusion can include

- damage to the liver with severe bleeding that may require blood transfusions or prolonged hospitalization.
- risk of viruses from the organ donor.
- the infusion may be stopped if the procedure increases pressure in the blood vessels of your liver. If this happens, all of the cells may not be infused.

You will need to take medicines that suppress your immune system regularly for your transplant to survive.

Risks of long-term immune suppression are increased risk of infection, including serious infection, organ failure, and death, and increased risk of certain cancers, including skin and lymph node cancer (lymphoma). Regular follow up appointments are needed.

Call your doctor right away if you have any symptoms of an infection, including:

- fever
- sweats or chills
- cough or flu-like symptoms
- muscle ache
- stiff neck
- warm, red, or painful areas on your skin
- confusion

Follow instructions for regular skin exams and notify your endocrinologist and transplant team if you are told you have skin cancer.

You will need to continue to take insulin and check your blood glucose (sugar) as instructed by your endocrinologist and transplant team.

Insulin independence is not immediate and can take several weeks to occur. Following treatment with LANTIDRA, not every patient becomes insulin independent and some patients who become insulin independent may need to restart insulin.

Monitor your blood glucose levels after getting LANTIDRA. Not all patients are able to stop taking insulin after getting the infusion. Do not stop taking insulin without talking to your doctor. It is very important to follow your doctor's instructions for blood glucose monitoring and keep your follow-up appointments to decrease the chance of serious and life-threatening high glucose or diabetic ketoacidosis.

What is LANTIDRA?

LANTIDRA is an islet cell therapy that is for people with Type 1 Diabetes. Islet cells come from the pancreas of a deceased organ donor.

Pancreatic islet cells include cells, called beta cells, that make insulin. In some people with Type 1 Diabetes, the infused beta cells can make enough insulin to allow the diabetic to control blood glucose without taking insulin.

Who should not take LANTIDRA?

LANTIDRA requires continuing use of medicines that suppress your immune system. Do not get the infusion if you cannot have these medicines because the islet cells will not survive.

Do not get LANTIDRA if you are pregnant or want to become pregnant. Immune suppression medicines can cause serious harm, including death, to you and your developing baby.

If you are male and have a female partner who can become or desires pregnancy, you should ask your transplant team if your immunosuppression drugs can cause abnormal sperm. If your immunosuppression drugs can cause abnormal sperm, advise your female partner to discuss the potential increased risks to her and the developing baby/infant with her healthcare provider.

How will I get LANTIDRA?

LANTIDRA islet cells are infused into your liver through a catheter that is placed into a large blood vessel going into your liver (called the hepatic portal vein). This is done under anesthesia. You will need to stay in the hospital for at least 24 hours.

Before getting LANTIDRA, you will need to start the immune suppression medicine. You will need to continue this medicine after the infusion to keep the islet cells alive.

What should I avoid when I get LANTIDRA?

Because immune suppression can increase your risk of infection, it is important that you:

- follow instructions from your transplant team about avoiding people who have infections, such as colds and flu.
- do not get immunization with live vaccines. Talk to your transplant team before getting any shots to prevent infections.

You can ask your transplant team if there are additional things you should avoid because of your specific immune suppression drugs.

What are the possible or reasonably likely side effects of LANTIDRA?

Injury can occur during the delivery of LANTIDRA into the large blood vessel going to your liver (the hepatic portal vein).

You have a higher risk of infections and cancer because of the immune suppression needed to keep the islet cells alive. In some cases, the immune suppression will be stopped because of these side effects and the islet cells will die and stop making insulin.

You can make antibodies from your islet cell infusion that can make it harder to get a match for transplants, such as a kidney transplant.

You can ask your doctor for information about LANTIDRA that is written for health professionals. Call your doctor about any side effects that concern you.

What should I tell my endocrinologist and transplant physician before receiving LANTIDRA?

For your LANTIDRA (islet cells) to survive, you must strictly follow the instructions for your immune suppression medicines. If you have any questions or problems about taking these medicines, ask your endocrinologist or transplant doctor for help.

If you can become pregnant, you should use effective birth control after getting LANTIDRA. Talk with your doctor about the birth control regimens that may be right for you.

Some immunosuppressive drugs may cause formation of abnormal sperm. Ask your doctor if your immunosuppression drugs can cause abnormal sperm. If so, and you have a female partner who can become pregnant, you should discuss this with your partner and use effective birth control before starting treatment with immunosuppression drugs.

What are the ingredients of LANTIDRA?

In addition to the cells in LANTIDRA the delivery fluid contains:

CaC12, anhydrous, biotin, MgSO4, anhydrous, folic acid, sodium acetate, anhydrous, riboflavin, NaH2PO4H2O, Cocarboxylase, dextrose, Li3 Coenzyme A 2 H2O, KCl, Cozymase, NaCl, Na2 Flavin adenine dinucleotide, Na Gluconate H2O, Na Triphosphopyridine Nucleotide, L-alanine, Na3 Uridine 5'-Triphosphoric Acid H2O, L-arginine HCl, ascorbic acid, L-aspartic acid, D-Ca-Pantothenate, L-cysteine HCl H2O, choline chloride, L-cystine 2 HCl, i-inositol, L-glutamic acid, nicotinic acid, glycine, nicotinamide, L-histidine HCl H2O, para-aminobenzoic acid, Hydroxy-L-proline, pyridoxine HCl, L-isoleucine, thiamine HCl, L-leucine, glutathione (reduced), L-lysine HCl, thymidine, L-methionine, 2D-adenosine, L-phenylalanine, 2D-cytidine HCl, L-proline, 2D-guanosine, L-serine, 5-methyl-2'- deoxycytidine, L-threonine, cholesterol, L-tryptophan, Tween 80, L-valine, L-alanyl-L-glutamine, L-tyrosine 2 Na 2 H2O

Name and Place of manufacturer:
CellTrans Inc.
1740 W. Taylor St., STE C200
Chicago, IL, 60612
24-Hour Contact Phone Number: 800-500-1617

PRINCIPAL DISPLAY PANEL - LANTIDRA Bag Label

donislecel – jujn
LANTIDRA
Allogeneic Pancreatic Islets, Cellular Suspension for Hepatic Portal Infusion.
Dose: One Sterile Bag of LANTIDRA for Primary Infusion followed by
One Sterile bag (Rinse) for secondary infusion

Rx Only

Lot Number: ______
Total EIN: ________

Manufactured Date:
YYYY–MMM–DD

Time
__:__

Product needs to be administered within 48 hours of product release time

For Use by Intended Recipient Only

Recipient Name: ________________
Recipient ID: ___________________
DOB: YYYY–MMM–DD
Recipient ABO/Rh: __/__

Do Not Use a Leukodepleting Filter
Do Not Irradiate
Storage at Room Temperaature (15°–25°C)
Transplant within expiration date and time,
LANTIDRA bag primary infusion

Target dose is 5,000 EIN/kg for initial transplant and
4,500 EIN/kg for subsequent transplants. LANTIDRA is a
cellular suspension of allogeneic pancreatic islets (Islets
of Langerhans) in buffered transplant media (See package
insert for complete list of transplant medium ingredients).

Donor Identifier
Donor ID: __________
DOB: YYYY–MMM–DD
Donor ABO/Rh: __/__

Dispose of Used Material that comes in
contact with LANTIDRA as biohazard
waste in accordance with local requirements

NDC 73539–001–01

Manufactured by: CellTrans Inc.
1740 W. Taylor St., STE C200,
Chicago, IL, 60612 (P: + 1 312 413 3507)

PRINCIPAL DISPLAY PANEL - RINSE Bag Label

Rinse Bag for Infusion following hepatic
portal infusion of LANTIDRA (Allogeneic
Pancreatic Islets for hepatic portal infusion)
Dose: One Sterile Bag of Rinse for Secondary
Infusion after primary infusion of LANTIDRA.

Rx Only

Lot Number: ______
Total EIN: ________

Manufactured Date:
YYYY–MMM–DD

Time
__:__

Product needs to be administered within 48 hours of product release time

Rinse Bag For Intended Recipient Only
(ONLY FOR USE WITH LANTIDRA)
Recipient Name: ________________
Recipient ID: ___________________
DOB: YYYY–MMM–DD
Recipient ABO/Rh: __/__

Do Not Use a Leukodepleting Filter
Do Not Irradiate
Storage at Room Temperaature (15°–25°C)
Transplant within expiration date and time
Rinse bag infused after the primary LANTIDRA
bag infusion and rinse goes through the LANTIDRA
CryoMACS bag

Target total volume of Rinse: 200 ml per bag. Transplant
media used for rinsing LANTIDRA CryoMACS bag to ensure
all islets are transfused. Rinse/Transplant media ingredient
list (See package insert for complete list of transplant
medium ingredients).

Dispose of Used Material that comes in
contact with LANTIDRA as biohazard
waste in accordance with local requirements

NDC 73539–002–01

Manufactured by: CellTrans Inc.
1740 W. Taylor St., STE C200,
Chicago, IL, 60612 (P: + 1 312 413 3507)

PRINCIPAL DISPLAY PANEL - Secondary Container Label

CONTENTS WITHIN THE OVERWRAP:

One sterile bag for Allogeneic Islet Cell
Suspension for hepatic portal infusion (LANTIDRA)
attached to one sterile bag for Rinse infusion.

PRINCIPAL DISPLAY PANEL - Carrier Label

Manufactured by: CellTrans Inc.
1740 W. Taylor St., STE C200.
Chicago, IL, 60612
Phone: +1 312 413 3507

Contents of Carrier System:
–LANTIDRA CryoMACS bag attached to Rinse CryoMACS bag within a primary and a secondary overwrap
–Package Insert
–Drape covers
–Tive Solo 5G Tracker
–TempTale Ultra, Temperature Data Logger

Accompanying Documentation:
–Donor Eligibility Determination Summary Records
–Final Islet Product Certificate of Analysis
–LANTIDRA Chain of Custody Form

Affixed Labels:
–LANTIDRA CryoMACS bag labels affixed to the CryoMACS bag containing the Allogeneic Islet Cell Suspension, to
the primary overwrap and to the secondary overwrap
–Rinse CryoMACS bag labels affixed to the CryoMACS bag containing 200 mL Transplant Media, to the primary
overwrap and to the secondary overwrap

Details of Transport:
The transport carrier containing LANTIDRA CryoMACS bag and Rinse CryoMACS bag is transported
from CellTrans to the receiving site for transplantation.